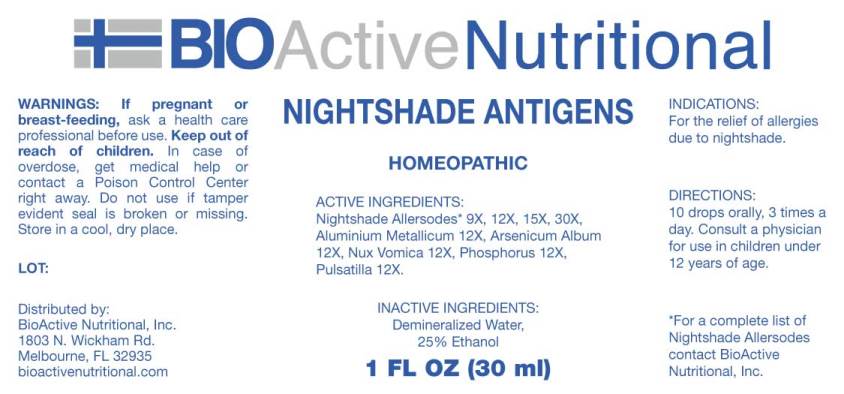 DRUG LABEL: Nightshade Antigen
NDC: 43857-0496 | Form: LIQUID
Manufacturer: BioActive Nutritional, Inc.
Category: homeopathic | Type: HUMAN OTC DRUG LABEL
Date: 20180925

ACTIVE INGREDIENTS: CAPSICUM 9 [hp_X]/1 mL; POTATO 9 [hp_X]/1 mL; TOBACCO LEAF 9 [hp_X]/1 mL; TOMATO 9 [hp_X]/1 mL; EGGPLANT 9 [hp_X]/1 mL; ALUMINUM 9 [hp_X]/1 mL; ARSENIC TRIOXIDE 12 [hp_X]/1 mL; STRYCHNOS NUX-VOMICA SEED 12 [hp_X]/1 mL; PHOSPHORUS 12 [hp_X]/1 mL; ANEMONE PRATENSIS 12 [hp_X]/1 mL
INACTIVE INGREDIENTS: WATER; ALCOHOL

Drug Facts:

ACTIVE INGREDIENTS:

Capsicum Annuum 9X, 12X, 15X, 30X, Solanum Tuberosum 9X, 12X, 15X, 30X, Tabacum 9X, 12X, 15X, 30X, Lycopersicum Esculentum 9X, 12X, 15X, 30X, Solanum Melongena 9X, 12X, 15X, 30X, Aluminum Metallicum 12X, Arsenicum Album 12X, Nux Vomica 12X, Phosphorus 12X, Pulsatilla (Pratensis) 12X.

INDICATIONS:

For the relief of allergies due to nightshade.

WARNINGS:

If pregnant or breast-feeding, ask a health care professional before use.
Keep out of reach of children. In case of overdose, get medical help or contact a Poison Control Center right away.
Do not use if tamper evident seal is broken or missing.
Store in cool, dry place.

Keep out of reach of children. In case of overdose, get medical help or contact a Poison Control Center right away.

DIRECTIONS:

10 drops orally, 3 times a day. Consult a physician for use in children under 12 years of age.

INDICATIONS:

For the relief of allergies due to nightshade.

INACTIVE INGREDIENTS:

Demineralized water, 25% Ethanol.

QUESTIONS:

Distributed by:

BioActive Nutritional, Inc.

1803 N. Wickham Rd.

Melbourne, FL 32935

bioactivenutritional.com

PACKAGE LABEL DISPLAY:

BIOActive Nutritional

NIGHTSHADE ANTIGENS

HOMEOPATHIC

1 FL OZ (30 ml)